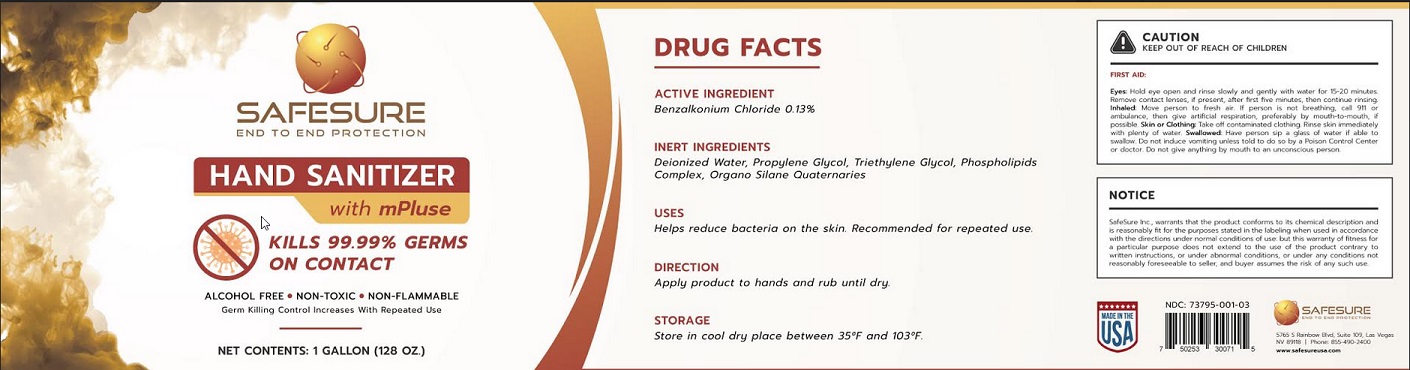 DRUG LABEL: Safesure hand sanitizer
NDC: 80852-001 | Form: LIQUID
Manufacturer: SAFE SURE USA, INC.
Category: otc | Type: HUMAN OTC DRUG LABEL
Date: 20201015

ACTIVE INGREDIENTS: BENZALKONIUM CHLORIDE 1.3 mg/1 mL
INACTIVE INGREDIENTS: WATER; PROPYLENE GLYCOL; TRIETHYLENE GLYCOL; PEG-75 LANOLIN; DIMETHYLOCTADECYL(3-(TRIMETHOXYSILYL)PROPYL)AMMONIUM CHLORIDE

Active Ingredient

Benzalkonium Chloride 1.3%

Use

Helps reduce bacteria on the skin. Recommended for repeated use.

Directions

Apply product to hands and rub until dry.

STORAGE
Store in cool dry place between 35°F and 103°F.

Inactive ingredients

Deionized Water, Propylene Glycol, Triethylene Glycol, Phospholipids Complex, Organo Silane Quaternaries